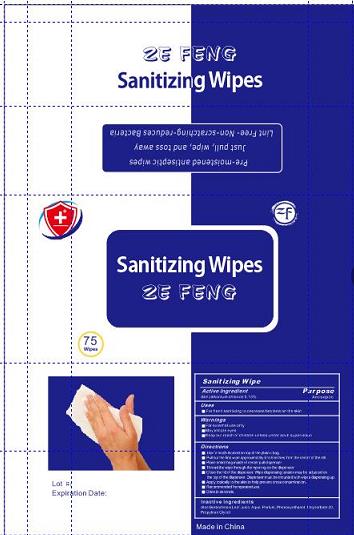 DRUG LABEL: Wet Wipe
NDC: 80332-001 | Form: CLOTH
Manufacturer: Quzhou Zefeng Import& Export Co., Ltd.
Category: otc | Type: HUMAN OTC DRUG LABEL
Date: 20200905

ACTIVE INGREDIENTS: BENZALKONIUM CHLORIDE 0.13 g/100 g
INACTIVE INGREDIENTS: WATER; POLYSORBATE 20; PROPYLENE GLYCOL; PHENOXYETHANOL

zefeng wet wipes 0.13% BENZALKONIUM CHLORIDE

Active Ingredient

Benzalkonium Chloride 0.13%

Purpose

Antimicrobial

USE

For hand washing to decrease bacteria on the skin.
Recommended for repeated use.

Warning

For external use only
When using this product, avoid contact with the eyes.
In case of contact, flush eyes thoroughly with water.
Stop use and ask a doctor if irritation and redness develop.

Keep out of reach of children. If swallowed, get medical help
or contact a Poison Control Center right away.

Directions

For hand sanitizing to decrease bacteria on the skin.
Recommended for repeated use.

Inactive ingredients

Aqua, Propylene Glycol, Polysorbate 20, Phenoxyethanol.

PACKAGE LABEL

75 PCS NDC 80332-001-01